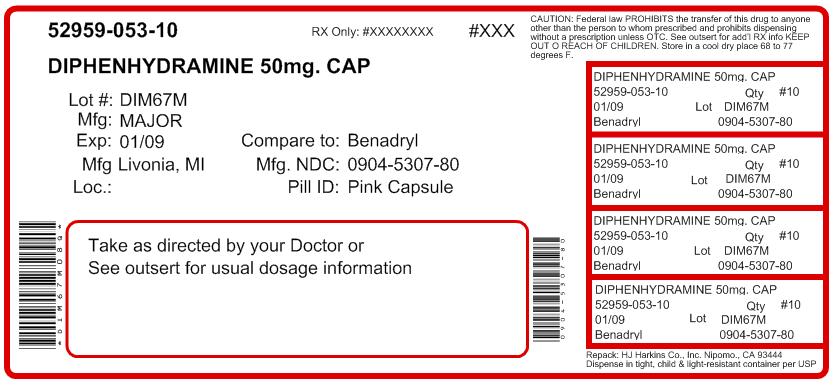 DRUG LABEL: Diphenhydramine
                        
NDC: 52959-053 | Form: CAPSULE
Manufacturer: H.J. Harkins Company, Inc.
Category: otc | Type: HUMAN OTC DRUG LABEL
Date: 20120418

ACTIVE INGREDIENTS: Diphenhydramine Hydrochloride 50 mg/1 1
INACTIVE INGREDIENTS: Gelatin; Lactose; Croscarmellose Sodium; Silicon Dioxide; FD&C RED NO. 40; Magnesium Stearate

Diphenhydramine Hydrochloride Capsules

Active ingredient

Diphenhydramine Hydrochloride 50mg

Purpose

Antihistamine

Use

Temporarily relieves these symptoms due to hay fever or other upper respiratory allergies and common cold, sneezing, runny nose, itchy, watery eyes, itchy throat and nose.

Warning

Ask a doctor before use if you have glaucoma, a breathing problem such as emphysema or chronic bronchitis, trouble urinating due to an enlarged prostate gland.

Ask a doctor or pharamcist before use if you are

taking tranquilizers or sedatives.

When using this product

you may get drowsy; avoid alcoholic drinks. Alcohol, sedatives and tranquilizers may increase drowsiness. Be careful when driving a motor vehicle or operating machinery. Excitability may occur, especially in children. Do not use any other products containing diphenhydramine.

Pregnancy/breast-feeding warning

If pregnant or breast-feeding, ask a health professional before use.

Keep out of reach of children. In case of overdose, get medical help or contact a Poison Control Center right away.

Directions

Adults and children 12 years and over: take 25 to 50 mg (1 to 2 capsule) every 4 to 6 hours; not more than 12 capsules in 24 hours.
Children 6 years to 12 years of age: take 25 mg (1 capsule) every 4 to 6 hours; not more than 6 capsules in 24 hours.
Children under 6 years of age: ask a doctor.

Other information

Store at controlled room temperature 59-86 degrees F.

Inactive ingredients

Lactose, starch, gelatin with bisulfites and artificial colors.

Questions?

Adverse drug event call: (800) 616-2471

Repacked by:

H.J. Harkins Company, Inc.

Grover Beach, CA 93433

Label